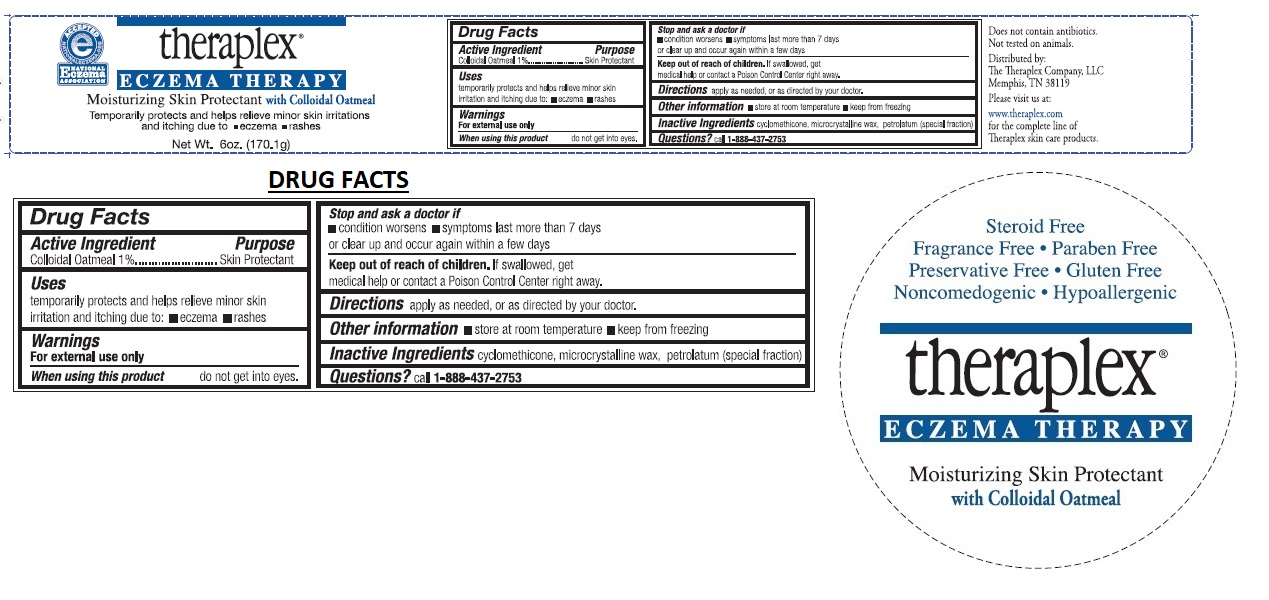 DRUG LABEL: Theraplex 
NDC: 62917-350 | Form: LOTION
Manufacturer: The Theraplex Company, LLC
Category: otc | Type: HUMAN OTC DRUG LABEL
Date: 20180222

ACTIVE INGREDIENTS: OATMEAL 1 g/100 g
INACTIVE INGREDIENTS: CYCLOMETHICONE; MICROCRYSTALLINE WAX; PETROLATUM

Theraplex

Active Ingredients

Colloidal Oatmeal 1%

Purpose

Skin Protectant

Uses

temporarily protects and helps relieve minor skin irritation and itching due to: • eczema • rashes

Warnings

For external use only.

When using this product do not get into eyes.

Stop use and ask a doctor if

• condition worsens • symptoms last more than 7 days or clear up and occur again within a few days.

Keep out of reach of children. If swallowed, get medical help or contact a Poison Control Center right away.

Directions

apply as needed, or as directed by your doctor.

Other information

• store at room temperature • keep from freezing

Inactive Ingredients

cyclomethicone,microcrystalline wax, petrolatum(special fraction)

Questions?

call 1-888-437-2753

Does not contain antibiotics.

Not tested on animals.

Distributed by:

The Theraplex Company, LLC

Memphis,TN 38119

Steroid Free

Fragrance Free

Paraben Free

Preservative Free

Gluten Free

Noncomedogenic

Hypoallergenic